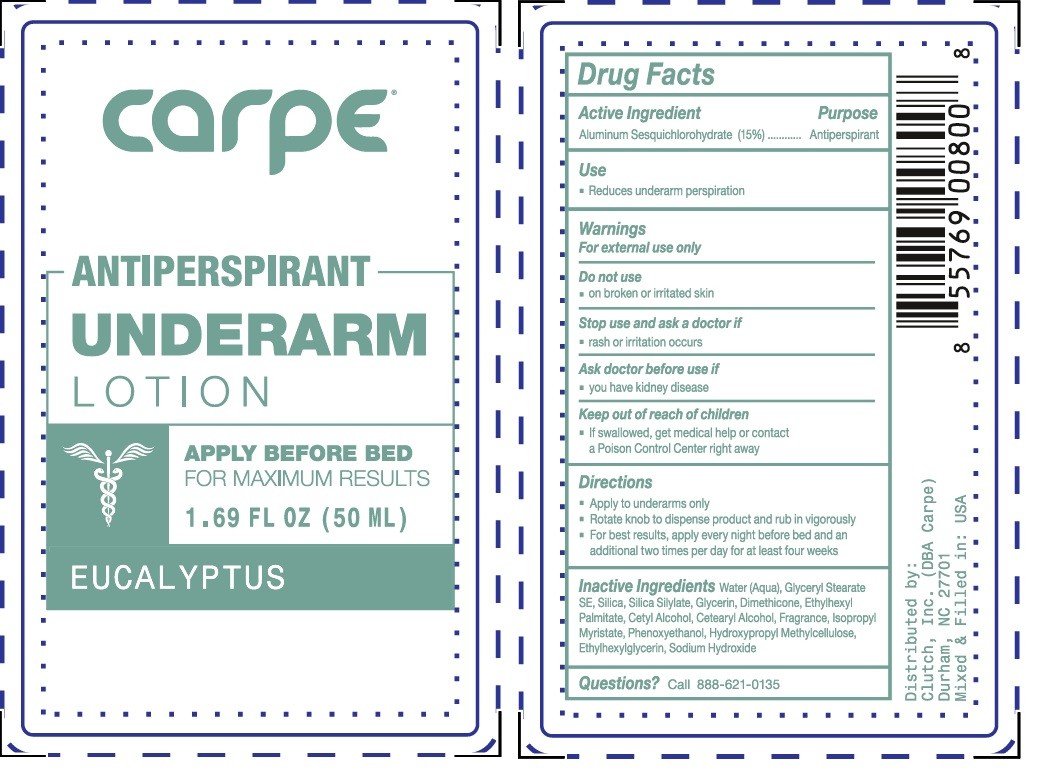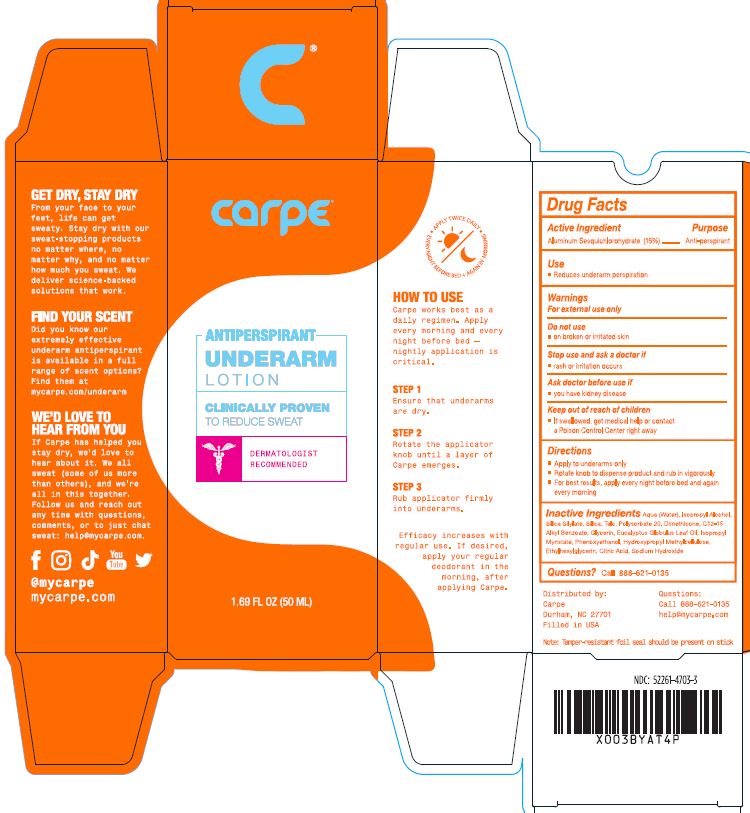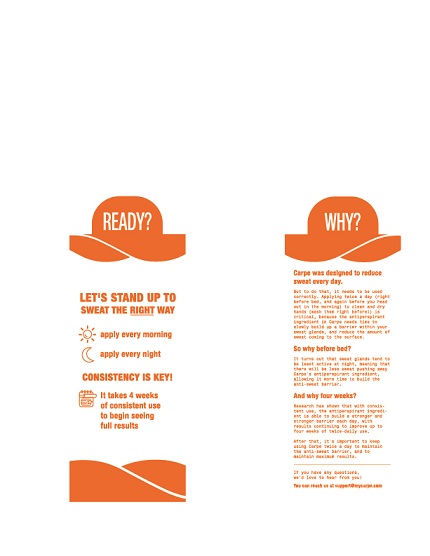 DRUG LABEL: Carpe Antiperspirant for Underarms
NDC: 52261-4703 | Form: Lotion
Manufacturer: Cosco International, Inc.
Category: otc | Type: HUMAN OTC DRUG LABEL
Date: 20250331

ACTIVE INGREDIENTS: Aluminum Sesquichlorohydrate 0.15048 kg/1 kg
INACTIVE INGREDIENTS: water; isopropyl alcohol; silicon dioxide; HEXAMETHYLDISILAZANE; talc; polysorbate 20; dimethicone 350; ALKYL (C12-15) BENZOATE; phenoxyethanol; ISOPROPYL MYRISTATE; eucalyptus oil; glycerin; hypromellose 2208 (60000 MPA.S); sodium hydroxide; citric acid monohydrate; ethylhexylglycerin

Drug Facts

Active IngredientPurpose
Aluminum Sesquicholorhydrate 15% .......................Antiperspirant

PURPOSE

Anti Perspirant

Use

- Reduces underarm perspiration

Warnings

For external use only

Do not use

- on broken or irritated skin

Stop use and ask a doctor if

- rash or irritation occurs

Ask doctor before use if

- you have kidney disease

Keep out of reach of children

- If swallowed, get medical help or contact a Poison Control Center right away

Directions

- Apply to underarms only
- Apply pea-sized amount to underarms and rub in vigorously
- For best results, apply every night before bed and an additional two times per day for at least four weeks

Inactive ingredients

Water, Isopropyl Alcohol, Silica, Silica Silylate, Talc, Polysorbate-20, Dimethicone, C12-15 Alkyl Benzoate, Phenoxyethanol, Isopropyl Myristate, Eucalyptus Oil, Glycerin, Hydroxypropyl Methylcellulose, Ethylhexylglycerin, Citric Acid, Sodium Hydroxide

Questions?

Call 888-621-0135

Distributed by: Carpe Durham, NC 27701 Made in: USA

Questions:

Call 888-621-0135

www.carpelotion.com